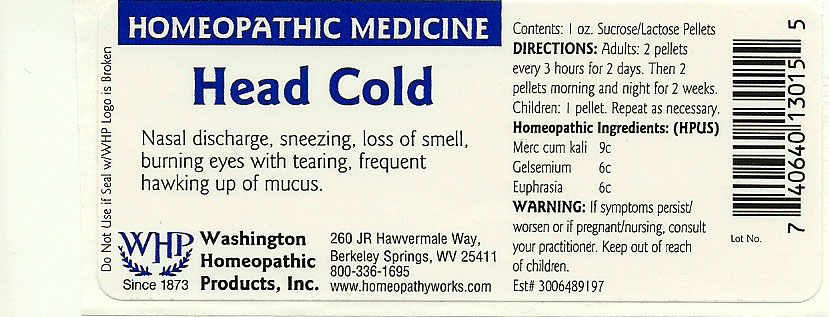 DRUG LABEL: Head Cold
NDC: 68428-019 | Form: PELLET
Manufacturer: Washington Homeopathic Products
Category: homeopathic | Type: HUMAN OTC DRUG LABEL
Date: 20151228

ACTIVE INGREDIENTS: POTASSIUM MERCURIC IODIDE 6 [hp_C]/1 1; GELSEMIUM SEMPERVIRENS ROOT 6 [hp_C]/1 1; EUPHRASIA STRICTA 6 [hp_C]/1 1
INACTIVE INGREDIENTS: SUCROSE; LACTOSE

DRUG FACTS

ACTIVE INGREDIENTS

MERC CUM KALI 6C

GELSEMIUM 6C

EUPHRASIA 6C

USES

To relieve the symptoms of nasal discharge, sneezing, loss of smell, burning eyes with tearing, frequent hawking up of mucus.

KEEP OUT OF REACH OF CHILDREN

Keep this and all medicines out of reach of children.

INDICATIONS

MERC CUM KALI Swollen glands

GELSEMIUM Lethargy

EUPHRASIA Eye irritation

STOP USE AND ASK DOCTOR

If symptoms persist/worsen or if pregnant/nursing, stop use and consult your practitioner.

DIRECTIONS

Adults 2 pellets every 3 hours for 2 days. Then 2 pellets morning and night for 2 weeks.

Children: 1 pellet. Repeat as necessary.

INACTIVE INGREDIENTS

Sucrose/Lactose

PRINCIPAL DISPLAY PANEL

Enter section text here